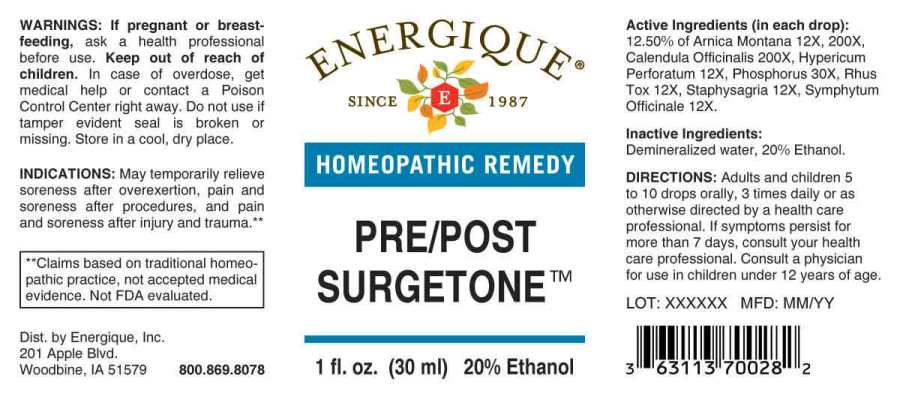 DRUG LABEL: Pre/Post Surgetone
NDC: 44911-0651 | Form: LIQUID
Manufacturer: Energique, Inc.
Category: homeopathic | Type: HUMAN OTC DRUG LABEL
Date: 20241029

ACTIVE INGREDIENTS: HYPERICUM PERFORATUM WHOLE 12 [hp_X]/1 mL; TOXICODENDRON PUBESCENS LEAF 12 [hp_X]/1 mL; DELPHINIUM STAPHISAGRIA SEED 12 [hp_X]/1 mL; COMFREY ROOT 12 [hp_X]/1 mL; ARNICA MONTANA WHOLE 12 [hp_X]/1 mL; PHOSPHORUS 30 [hp_X]/1 mL; CALENDULA OFFICINALIS FLOWERING TOP 200 [hp_X]/1 mL
INACTIVE INGREDIENTS: WATER; ALCOHOL

DRUG FACTS:

ACTIVE INGREDIENTS:

(in each drop): 12.50% of Arnica Montana12X, 200X, Calendula Officinalis 200X, Hypericum Perforatum 12X, Phosphorus 30X, Rhus Tox 12X, Staphysagria 12X, Symphytum Officinale 12X.

INDICATIONS:

May temporarily relieve soreness after overexertion, pain and soreness after procedures, and pain and soreness after injury and trauma.**

**Claims based on traditional homeopathic practice, not accepted medical evidence. Not FDA evaluated.

WARNINGS:

If pregnant or breast-feeding, ask a health professional before use.

Keep out of reach of children. In case of overdose, get medical help or contact a Poison Control Center right away.

Do not use if tamper evident seal is broken or missing.

Store in a cool, dry place.

Keep out of reach of children. In case of overdose, get medical help or contact a Poison Control Center right away.

DIRECTIONS:

Adults and children 5 to 10 drops orally, 3 times daily or as otherwise directed by a health care professional. If symptoms persist for more than 7 days, consult your health care professional. Consult a physician for use in children under 12 years of age.

INDICATIONS:

May temporarily relieve soreness after overexertion, pain and soreness after procedures, and pain and soreness after injury and trauma.**

**Claims based on traditional homeopathic practice, not accepted medical evidence. Not FDA evaluated.

INACTIVE INGREDIENTS:

Demineralized water, 20% Ethanol

QUESTIONS:

Dist. by Energique, Inc.

201 Apple Blvd

Woodbine, IA 51579 800-869-8078

PACKAGE LABEL DISPLAY:

ENERGIQUE

SINCE 1987

HOMEOPATHIC REMEDY

PRE/POST SURGETONE

1 fl. oz. (30 ml)